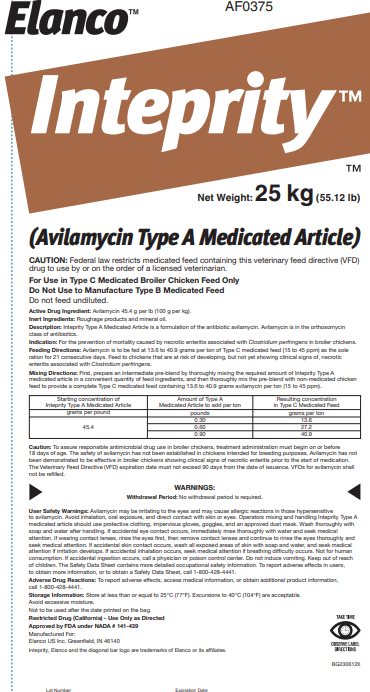 DRUG LABEL: Inteprity
NDC: 58198-0375 | Form: GRANULE
Manufacturer: Elanco US Inc.
Category: animal | Type: VFD TYPE A MEDICATED ARTICLE ANIMAL DRUG LABEL
Date: 20251121

ACTIVE INGREDIENTS: avilamycin 100 g/1 kg

Elanco™ AF0375

Inteprity™

Net Weight: 25 kg (55.12 lb)

(Avilamycin Type A Medicated Article)

CAUTION: Federal law restricts medicated feed containing this veterinary feed directive (VFD) drug to use by or on the order of a licensed veterinarian.

For Use in Type C Medicated Broiler Chicken Feed Only

Do Not Use to Manufacture Type B Medicated Feed

Do not feed undiluted.

Active Drug Ingredient: Avilamycin 45.4 g per lb (100 g per kg).

Inert Ingredients: Roughage products and mineral oil.

Description:

Inteprity Type A Medicated Article is a formulation of the antibiotic avilamycin. Avilamycin is in the orthosomycin class of antibiotics.

Indication:

For the prevention of mortality caused by necrotic enteritis associated with Clostridium perfringens in broiler chickens.

Feeding Directions:

Avilamycin is to be fed at 13.6 to 40.9 grams per ton of Type C medicated feed (15 to 45 ppm) as the sole ration for 21 consecutive days. Feed to chickens that are at risk of developing, but not yet showing clinical signs of, necrotic enteritis associated with Clostridium perfringens.

Mixing Directions:

First, prepare an intermediate pre-blend by thoroughly mixing the required amount of Inteprity Type A medicated article in a convenient quantity of feed ingredients, and then thoroughly mix the pre-blend with non-medicated chicken feed to provide a complete Type C medicated feed containing 13.6 to 40.9 grams avilamycin per ton (15 to 45 ppm).

Starting concentration of Inteprity Type A Medicated Article | Amount of Type A Medicated Article to add per ton | Resulting concentration in Type C Medicated Feed
grams per pound | pounds | grams per ton
45.4 | 0.30 | 13.6
45.4 | 0.60 | 27.2
45.4 | 0.90 | 40.9

Caution: To assure responsible antimicrobial drug use in broiler chickens, treatment administration must begin on or before 18 days of age. The safety of avilamycin has not been established in chickens intended for breeding purposes. Avilamycin has not been demonstrated to be effective in broiler chickens showing clinical signs of necrotic enteritis prior to the start of medication. The Veterinary Feed Directive (VFD) expiration date must not exceed 90 days from the date of issuance. VFDs for avilamycin shall not be refilled.

WARNINGS:

Withdrawal Period: No withdrawal period is required.

User Safety Warnings: Avilamycin may be irritating to the eyes and may cause allergic reactions in those hypersensitive to avilamycin. Avoid inhalation, oral exposure, and direct contact with skin or eyes. Operators mixing and handling Inteprity Type A medicated article should use protective clothing, impervious gloves, goggles, and an approved dust mask. Wash thoroughly with soap and water after handling. If accidental eye contact occurs, immediately rinse thoroughly with water and seek medical attention. If wearing contact lenses, rinse the eyes first, then remove contact lenses and continue to rinse the eyes thoroughly and seek medical attention. If accidental skin contact occurs, wash all exposed areas of skin with soap and water, and seek medical attention if irritation develops. If accidental inhalation occurs, seek medical attention if breathing difficulty occurs. Not for human consumption. If accidental ingestion occurs, call a physician or poison control center. Do not induce vomiting. Keep out of reach of children. The Safety Data Sheet contains more detailed occupational safety information. To report adverse effects in users, to obtain more information, or to obtain a Safety Data Sheet, call 1-800-428-4441.

Adverse Drug Reactions:

To report adverse effects, access medical information, or obtain additional product information, call 1-800-428-4441.

Storage Information:

Store at less than or equal to 25°C (77°F). Excursions to 40°C (104°F) are acceptable.

Avoid excessive moisture.

Not to be used after the date printed on the bag.

Restricted Drug (California) - Use Only as Directed

Approved by FDA under NADA # 141-439

Manufactured For:
Elanco US Inc. Greenfield, IN 46140

Inteprity, Elanco and the diagonal bar logo are trademarks of Elanco or its affiliates.

TAKE TIME
OBSERVE LABEL
DIRECTIONS

BG230612X

Lot Number Expiration Date

Principal Display Panel – 25 kg Bag Label

Elanco™

AF0375

Inteprity™

Net Weight: 25 kg (55.12 lb)
(Avilamycin Type A Medicated Article)